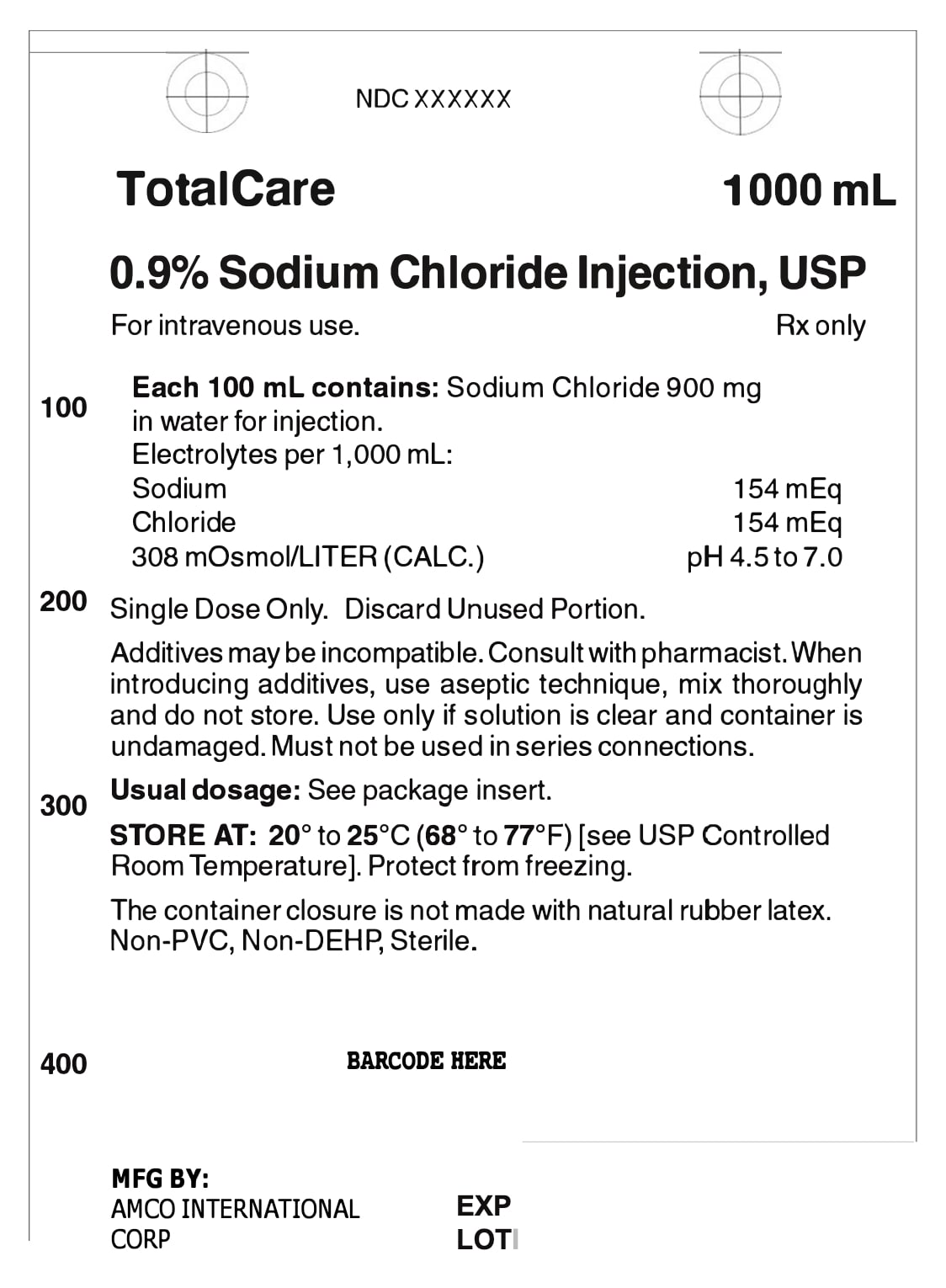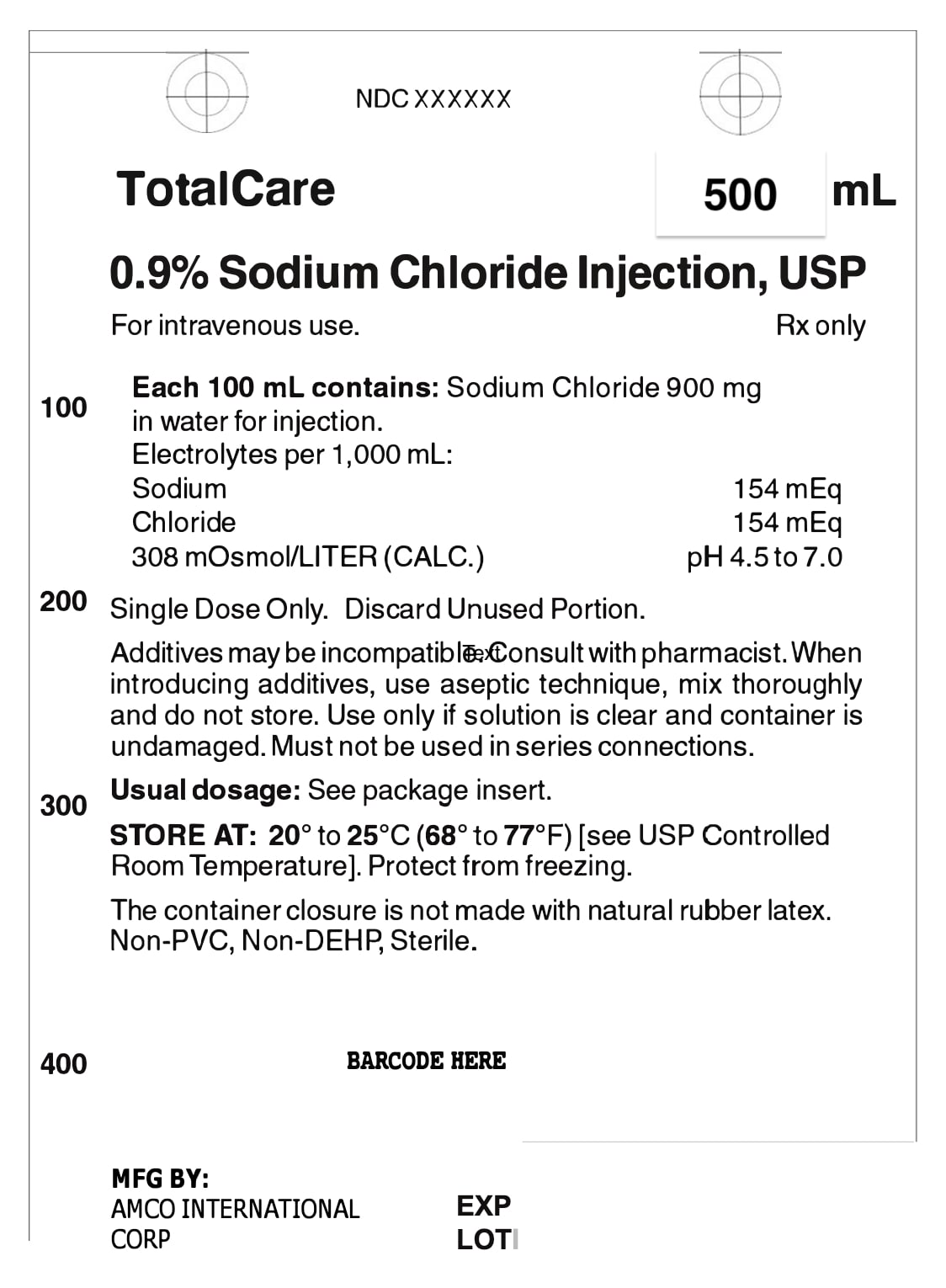 DRUG LABEL: 0.9% Sodium Chloride Injection, 1000mL, Blue Pharma, TotalCare
NDC: 84866-6669 | Form: INJECTION, SOLUTION
Manufacturer: AMCO INTERNATIONAL CORP
Category: prescription | Type: HUMAN PRESCRIPTION DRUG LABEL
Date: 20241126

ACTIVE INGREDIENTS: SODIUM CHLORIDE 9 mg/1 mL
INACTIVE INGREDIENTS: WATER

DESCRIPTION

0.9% Sodium Chloride Injection, USP solution is sterile and nonpyrogenic. It is a parenteral solution containing sodium chloride in water for injection intended for intravenous administration.

For 0.9% Sodium Chloride Injection, USP, each 100 mL contains 900 mg sodium chloride in water for injection. Electrolytes per 1,000 mL: sodium 154 mEq; chloride 154 mEq. The osmolarity is 308 mOsmol/L (calc.).

The pH in the 100 mL and smaller containers is 6.0; for the 250 mL and larger containers, the pH is 5.6. The pH range is 4.5 to 7.0 for all containers.

The solution contains no bacteriostat, antimicrobial agent or added buffer and is intended only as a single-dose injection. When smaller doses are required the unused portion should be discarded.

The solution is a parenteral fluid and electrolyte replenisher.
Sodium Chloride, USP is chemically designated NaCl, a white crystalline powder freely soluble in water. Water for injection, USP is chemically designated H2O.

The flexible container is fabricated from a specially formulated non-plasticized, film containing polypropylene and thermoplastic elastomers. The bag has a needle-free injection port and can accept standard luer lock syringes to add medication. The amount of water that can permeate from the container into the overwrap is insufficient to affect the solution significantly. Solutions in contact with the flexible container can leach out certain of the container's chemical components in very small amounts within the expiration period. The suitability of the container material has been confirmed by tests in animals according to USP biological tests for plastic containers.

CLINICAL PHARMACOLOGY

When administered intravenously, the solution provides a source of water and electrolytes.

Solutions which provide combinations of hypotonic or isotonic concentrations of sodium chloride are suitable for parenteral maintenance or replacement of water and electrolyte requirements.

Isotonic concentrations of sodium chloride are suitable for parenteral replacement of chloride losses that exceed or equal the sodium loss. Hypotonic concentrations of sodium chloride are suited for parenteral maintenance of water requirements when only small quantities of salt are desired. A hypertonic concentration of sodium chloride may be used to repair severe salt depletion syndrome.

Sodium chloride in water dissociates to provide sodium (Na+) and chloride (Cl-) ions. Sodium (Na+) is the principal cation of the extracellular fluid and plays a large part in the therapy of fluid and electrolyte disturbances. Chloride (Cl-) has an integral role in buffering action when oxygen and carbon dioxide exchange occurs in the red blood cells. The distribution and excretion of sodium (Na+) and chloride (Cl-) are largely under the control of the kidney which maintains a balance between intake and output.

Water is an essential constituent of all body tissues and accounts for approximately 70% of total body weight. Average normal adult daily requirements range from two to three liters (1.0 to 1.5 liters each for insensible water loss by perspiration and urine production).

Water balance is maintained by various regulatory mechanisms. Water distribution depends primarily on the concentration of electrolytes in the body compartments and sodium (Na+) plays a major role in maintaining physiologic equilibrium.

INDICATIONS AND USAGE

Intravenous solutions containing sodium chloride are indicated for parenteral replenishment of fluid and sodium chloride as required by the clinical condition of the patient.

CONTRAINDICATIONS

None known.

WARNINGS AND PRECAUTIONS

Sodium Chloride Injection, USP should be used with great care, if at all, in patients with congestive heart failure, severe renal insufficiency and in clinical states in which there exists edema with sodium retention.

The intravenous administration of Sodium Chloride Injection, USP can cause fluid and/or solute overloading resulting in dilution of serum electrolyte concentrations, overhydration, congested states or pulmonary edema.

The risk of dilutive states is inversely proportional to the electrolyte concentration of the injections. The risk of solute overload causing congested states with peripheral and pulmonary edema is directly proportional to the electrolyte concentrations of the injections.

In patients with diminished renal function, administration of Sodium Chloride Injection, USP may result in sodium retention.

General

Do not use plastic containers in series connections. Such use could result in air embolism due to residual air being drawn from the primary container before administration of the fluid from the secondary container is completed.

Pressurizing intravenous solutions contained in flexible plastic containers to increase flow rates can result in air embolism if the residual air in the container is not fully evacuated prior to administration.

Use of a vented intravenous administration set with the vent in the open position could result in air embolism. Vented intravenous administration sets with the vent in the open position should not be used with flexible plastic containers.

Laboratory Tests

Clinical evaluation and periodic laboratory determinations are necessary to monitor changes in fluid balance, electrolyte concentrations and acid-base balance during prolonged parenteral therapy or whenever the condition of the patient warrants such evaluation.

DRUG INTERACTIONS

Caution must be exercised in the administration of Sodium Chloride Injection, USP to patients receiving corticosteroids or corticotropin.

Carcinogenesis, Mutagenesis, Impairment of Fertility

PREGNANCY

Teratogenic Effects

Pregnancy Category C

Animal reproduction studies have not been conducted with Sodium Chloride Injection, USP. It is also not known whether Sodium Chloride Injection, USP can cause fetal harm when administered to a pregnant woman or can affect reproduction capacity. Sodium Chloride Injection, USP should be given to a pregnant woman only if clearly needed.

NURSING MOTHERS

It is not known whether this drug is excreted in human milk. Because many drugs are excreted in human milk, caution should be exercised when Sodium Chloride Injection, USP is administered to a nursing mother.

LABOR AND DELIVERY

Studies have not been conducted to evaluate the effects of Sodium Chloride Injection, USP on labor and delivery. Caution should be exercised when administrating this drug during labor and delivery.

PEDIATRIC USE

The use of Sodium Chloride Injection, USP in pediatric patients is based on clinical practice.

Plasma electrolyte concentrations should be closely monitored in the pediatric population as this population may have impaired ability to regulate fluids and electrolytes.

GERIATRIC USE

Clinical studies of Sodium Chloride Injection, USP did not include sufficient numbers of subjects aged 65 and over to determine whether they respond differently from younger subjects. Other reported clinical experience has not identified differences in responses between elderly and younger patients. In general, dose selection for an elderly patient should be cautious, usually starting at the low end of the dosing range, reflecting the greater frequency of decreased hepatic, renal, or cardiac function, and of concomitant disease or drug therapy.

This drug is known to be substantially excreted by the kidney, and the risk of toxic reactions to this drug may be greater in patients with impaired renal function. Because elderly patients are more likely to have decreased renal function, care should be taken in dose selection, and it may be useful to monitor renal function.

Do not administer unless solution is clear and container is undamaged. Discard unused portion.

ADVERSE REACTIONS

Reactions which may occur because of the solution or the technique of administration include febrile response, infection at the site of injection, venous thrombosis or phlebitis extending from the site of injection, extravasation and hypervolemia.

If an adverse reaction does occur, discontinue the infusion, evaluate the patient, institute appropriate therapeutic countermeasures and save the remainder of the fluid for examination if deemed necessary.

OVERDOSAGE

In the event of overhydration or solute overload, re-evaluate the patient and institute appropriate corrective measures (see WARNINGS, PRECAUTIONS, and ADVERSE REACTIONS).

DOSAGE AND ADMINISTRATION

The dose is dependent upon the age, weight and clinical condition of the patient.
Additives may be incompatible. Consult with pharmacist, if available. When introducing additives, use aseptic technique, mix thoroughly and do not store.

Parenteral drug products should be inspected visually for particulate matter and discoloration prior to administration, whenever solution and container permit (see PRECAUTIONS).

INSTRUCTIONS FOR USE

Check flexible container solution composition, lot number, and expiry date.
Do not remove solution container from its overwrap until immediately before use. Use sterile equipment and aseptic technique.

To Open

1. Turn solution container over so that the text is face down. Using the pre-cut corner tabs, peel open the overwrap and remove solution container. 2. Check the solution container for leaks by squeezing firmly. If leaks are found, or if the seal is not intact, discard the solution.
3. Do not use if the solution is cloudy or a precipitate is present.

To Add Medication

The Additive port of the container accepts standard luer lock syringes. Do not use a needle for additions.
1. Identify LIGHT BLUE Additive Port with arrow pointing toward solution container.
2. Immediately before injecting additives, break off LIGHT BLUE Additive Port Cap with the arrow pointing toward solution container. 3. Hold base of LIGHT BLUE Additive Port.
4. Attach Luer Lock syringe to the threaded LIGHT BLUE Additive Port. Inject additive.
5. Mix solution container contents thoroughly.

Preparation for Administration

1. Immediately before inserting the infusion set, break off BLUE Infusion Port Cap with the arrow pointing away from container. 2. Use a non-vented infusion set or close the air-inlet on a vented set.
3. Close the roller clamp of the infusion set.
4. Hold the base of BLUE Infusion Port.

5. Insert spike through BLUE Infusion Port by rotating wrist slightly until the spike is inserted. NOTE: See full directions accompanying administration set.

WARNING: Do not use flexible container in series connections.

HEALTH CARE PROVIDER LETTER

Important Prescribing Information

Subject: Marketing of Pending Approval 0.9% Sodium Chloride Injection to address drug shortages

Dear Healthcare Professional,

To prevent a drug shortage of large volume parenteral fluid drug products, we are
coordinating with the U.S. Food and Drug Administration (FDA) to temporarily import 0.9% Sodium Chloride Injection
(250 mL; 500 mL and 1,000 mL) from specific DRE manufacturing facilities. FDA has not approved these
products manufactured by this facility.

You may be provided with additional letters for other imported products you receive. Please read each letter in its
entirety because each letter may contain different product specific information.

Effective immediately, and during this temporary period, we will offer the following imported products:

It is important to note the following:
• After opening the carton or box, the bags should be inspected visually to confirm there is no visible particulate
matter or bag defects, such as leaks. Container integrity is imperative to ensure sterility of products listed in the
table above. Parenteral drug products should be inspected visually for particulate matter and bag defects prior to
administration, whenever solution or container permits.
USE A NEW BAG IF PARTICULATES ARE VISIBLE OR IF THE IV BAG CONTAINS A LEAK.

Reporting Adverse Events or Product Quality Issues
To report adverse events associated with these imported products, please call

. Adverse events or quality problems experienced with the use of these imported products may also be
reported to the FDA's MedWatch Adverse Event Reporting program either online, by regular mail or by fax:
• Complete and submit the report Online: www.fda.gov/medwatch/report.htm
• Regular mail or Fax: Download form www.fda.gov/MedWatch/getforms.htm or call 1-800-332-1088 to
request a reporting form, then complete and return to the address on the pre-addressed form, or submit by
fax to 1-800-FDA-0178 (1-800-332-0178).

To report product quality issues associated with these imported products, please contact

If you have any questions about the information contained in this letter or the use of the imported products, please
contact

To place an order, please contact

PACKAGE LABEL - PRINCIPAL DISPLAY – 0.9% Sodium Chloride 1000 mL Bag Label

Each 100 ml contains: Sodium Chloride 900 mg in water for injection.

[NDC 84866-6667-1]

DRE HEALTH TotalCare
For intravenous use. Rx only

1 000ml 0.9% Sodium Chloride Injection, USP

Electrolytes per 1,000 ml:

Sodium
Chloride
308 mOsmol/LITER (CALC.)

SingleDoseOnly. DiscardUnusedPortion.

154 mEq

154 mEq pH 4.5to 7.0

Additives may be incompatible. Consult with pharmacist. When introducing additives, use aseptic technique, mux thoroughly and do not store. Use only if solution is clear and container is undamaged. Must not be used in series connections.

Usual dosage: See package insert. °°°°

STORE AT: 20 to 25 C (68 to 77 F) [see USP Controlled RoomTemperature].Protectfromfreezing.

The container closure is not made with natural rubber latex. Non-PVC, Non-DEHP, Sterile.

MFG BY: AMCO INTERNATIONAL CORP

EXP. LOT.

[BARCODE HERE]

PACKAGE LABEL - PRINCIPAL DISPLAY – 0.9% Sodium Chloride 500 mL Bag Label

Each 100 ml contains: Sodium Chloride 900 mg in water for injection.

[NDC 84866-6681-1]

DRE BioLab TotalCare
For intravenous use. Rx only

500ml 0.9% Sodium Chloride Injection, USP

Electrolytes per 1,000 ml:

Sodium
Chloride
308 mOsmol/LITER (CALC.)

SingleDoseOnly. DiscardUnusedPortion.

154 mEq

154 mEq pH 4.5to 7.0

Additives may be incompatible. Consult with pharmacist. When introducing additives, use aseptic technique, mux thoroughly and do not store. Use only if solution is clear and container is undamaged. Must not be used in series connections.

Usual dosage: See package insert. °°°°

STORE AT: 20 to 25 C (68 to 77 F) [see USP Controlled RoomTemperature].Protectfromfreezing.

The container closure is not made with natural rubber latex. Non-PVC, Non-DEHP, Sterile.

MFG BY: AMCO INTERNATIONAL CORP

EXP. LOT.

[BARCODE HERE]

PACKAGE LABEL - PRINCIPAL DISPLAY – 0.9% Sodium Chloride 500 mL Case Label

Each 100 ml contains: Sodium Chloride 900 mg in water for injection.

[NDC 84866-6681-2]

DRE BioLab TotalCare
For intravenous use. Rx only

500ml 0.9% Sodium Chloride Injection, USP

Electrolytes per 1,000 ml:

Sodium
Chloride
308 mOsmol/LITER (CALC.)

SingleDoseOnly. DiscardUnusedPortion.

154 mEq

154 mEq pH 4.5to 7.0

Additives may be incompatible. Consult with pharmacist. When introducing additives, use aseptic technique, mux thoroughly and do not store. Use only if solution is clear and container is undamaged. Must not be used in series connections.

Usual dosage: See package insert. °°°°

STORE AT: 20 to 25 C (68 to 77 F) [see USP Controlled RoomTemperature].Protectfromfreezing.

The container closure is not made with natural rubber latex. Non-PVC, Non-DEHP, Sterile.

MFG BY: AMCO INTERNATIONAL CORP

EXP. LOT.

[BARCODE HERE]

PACKAGE LABEL - PRINCIPAL DISPLAY – 0.9% Sodium Chloride 1000 mL Case Label

Each 100 ml contains: Sodium Chloride 900 mg in water for injection.

[NDC 84866-6666-2]

DRE BioLab TotalCare
For intravenous use. Rx only

500ml 0.9% Sodium Chloride Injection, USP

Electrolytes per 1,000 ml:

Sodium
Chloride
308 mOsmol/LITER (CALC.)

SingleDoseOnly. DiscardUnusedPortion.

154 mEq

154 mEq pH 4.5to 7.0

Additives may be incompatible. Consult with pharmacist. When introducing additives, use aseptic technique, mux thoroughly and do not store. Use only if solution is clear and container is undamaged. Must not be used in series connections.

Usual dosage: See package insert. °°°°

STORE AT: 20 to 25 C (68 to 77 F) [see USP Controlled RoomTemperature].Protectfromfreezing.

The container closure is not made with natural rubber latex. Non-PVC, Non-DEHP, Sterile.

MFG BY: AMCO INTERNATIONAL CORP

EXP. LOT.

[BARCODE HERE]

PACKAGE LABEL - PRINCIPAL DISPLAY – 0.9% Sodium Chloride 1000 mL Case Label

Each 100 ml contains: Sodium Chloride 900 mg in water for injection.

[NDC 84866-6667-2]

DRE BioLab TotalCare
For intravenous use. Rx only

500ml 0.9% Sodium Chloride Injection, USP

Electrolytes per 1,000 ml:

Sodium
Chloride
308 mOsmol/LITER (CALC.)

SingleDoseOnly. DiscardUnusedPortion.

154 mEq

154 mEq pH 4.5to 7.0

Additives may be incompatible. Consult with pharmacist. When introducing additives, use aseptic technique, mux thoroughly and do not store. Use only if solution is clear and container is undamaged. Must not be used in series connections.

Usual dosage: See package insert. °°°°

STORE AT: 20 to 25 C (68 to 77 F) [see USP Controlled RoomTemperature].Protectfromfreezing.

The container closure is not made with natural rubber latex. Non-PVC, Non-DEHP, Sterile.

MFG BY: AMCO INTERNATIONAL CORP

EXP. LOT.

[BARCODE HERE]

PACKAGE LABEL - PRINCIPAL DISPLAY – 0.9% Sodium Chloride 1000 mL Bag Label

Each 100 ml contains: Sodium Chloride 900 mg in water for injection.

[NDC 84866-6666-1]

DRE HEALTH TotalCare
For intravenous use. Rx only

1 000ml 0.9% Sodium Chloride Injection, USP

Electrolytes per 1,000 ml:

Sodium
Chloride
308 mOsmol/LITER (CALC.)

SingleDoseOnly. DiscardUnusedPortion.

154 mEq

154 mEq pH 4.5to 7.0

Additives may be incompatible. Consult with pharmacist. When introducing additives, use aseptic technique, mux thoroughly and do not store. Use only if solution is clear and container is undamaged. Must not be used in series connections.

Usual dosage: See package insert. °°°°

STORE AT: 20 to 25 C (68 to 77 F) [see USP Controlled RoomTemperature].Protectfromfreezing.

The container closure is not made with natural rubber latex. Non-PVC, Non-DEHP, Sterile.

MFG BY: AMCO INTERNATIONAL CORP

EXP. LOT.

[BARCODE HERE]